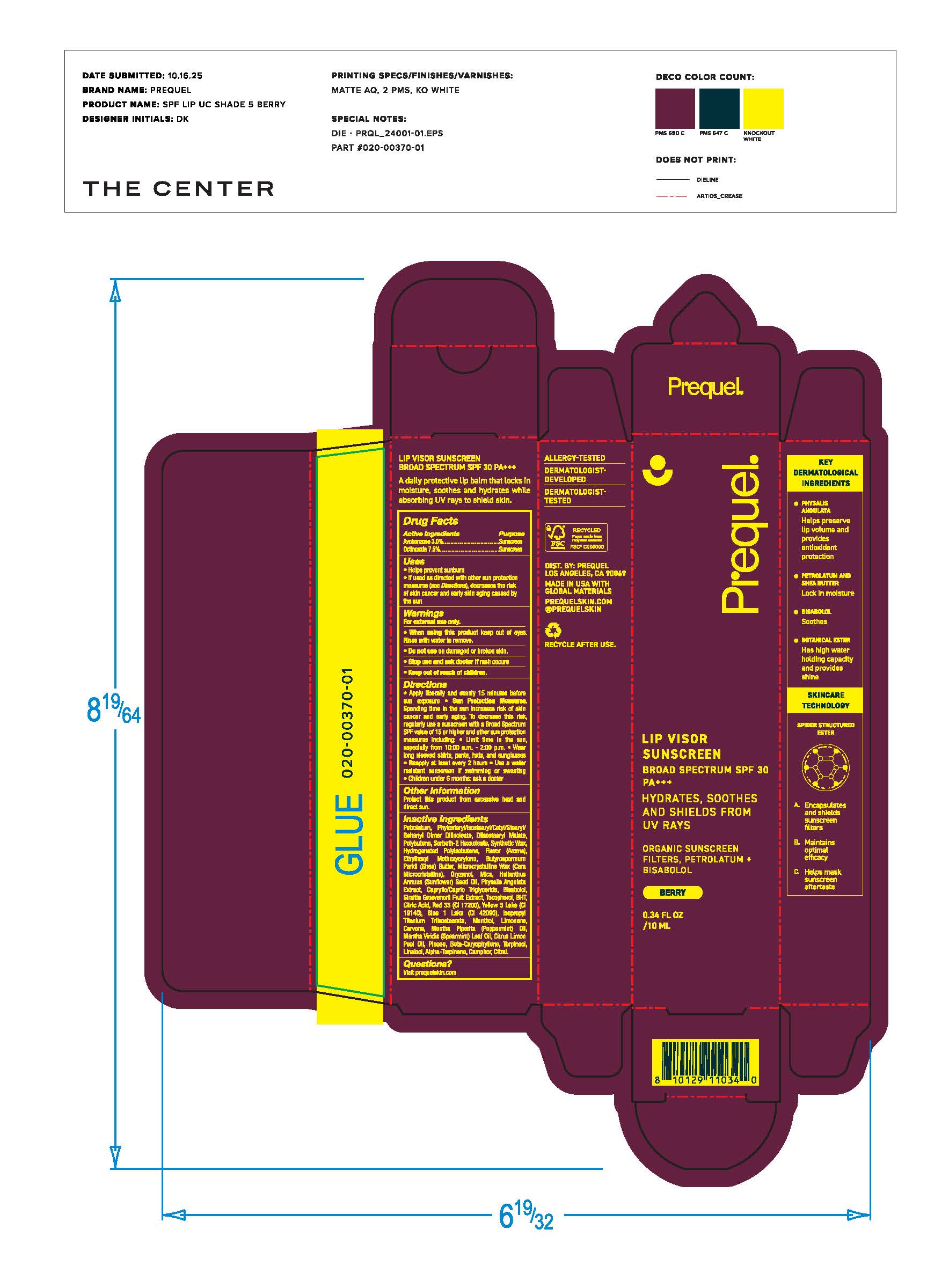 DRUG LABEL: Prequel Lip Visor Berry SPF 30
NDC: 82800-110 | Form: LIPSTICK
Manufacturer: The Center Brands, LLC
Category: otc | Type: HUMAN OTC DRUG LABEL
Date: 20260116

ACTIVE INGREDIENTS: AVOBENZONE 3 mg/100 mg; OCTINOXATE 7.5 mg/100 mg
INACTIVE INGREDIENTS: RED 33; LINALOOL; ISOPROPYL TITANIUM TRIISOSTEARATE; LIMONENE, (+)-; SYNTHETIC WAX (1200 MW); CARVONE; TERPINEOL; SIRAITIA GROSVENORII LEAF; YELLOW 5; MENTHOL; MENTHA VIRIDIS (SPEARMINT) LEAF OIL; PETROLATUM; PHYTOSTERYL/ISOSTEARYL/CETYL/STEARYL/BEHENYL DIMER DILINOLEATE; DIISOSTEARYL MALATE; POLYBUTENE (1400 MW); SORBETH-2 HEXAOLEATE; HYDROGENATED POLYISOBUTENE (450 MW); ETHYLHEXYL METHOXYCRYLENE; BUTYROSPERMUM PARKII (SHEA) BUTTER; MICROCRYSTALLINE WAX; ORYZANOL; MICA; HELIANTHUS ANNUUS SEED WAX; PHYSALIS ANGULATA WHOLE; CAPRYLIC/CAPRIC TRIGLYCERIDE; BETA-CARYOPHYLLENE; TOCOPHEROL; CITRAL; BISABOLOL; BHT; PINENE; CITRUS LIMON SEED OIL; CAMPHOR, (-)-; BLUE 1 LAKE; CITRIC ACID; MENTHA PIPERITA (PEPPERMINT) OIL; ALPHA-TERPINENE

Prequel Lip Visor Berry SPF 30

Active Ingredients

Avobenzone 3.0%

Octinoxate 7.5%

Uses

• helps prevent sunburn • if used as directed with other
sun protection measures (see Directions), decreases the
risk of skin cancer and early skin aging caused by the sun

Warnings

For external use only
Do not use on damaged or broken skin.
When using this product keep out of eyes. Rinse with water to remove.
Stop use and ask a docor if rash occurs
Keep out of reach of children. If swalled, get medical help or contact a Poison Control Center right away.

Directions

• apply liberally and evenly15 minutes before sun exposure

• Sun Protection Measures. Spending time in the sun

increases your risk of skin cancer and early skin aging. To decrease
this risk, regularly use a sunscreen with a Broad Spectrum SPF
value of 15 or higher and other sun protection measures including:
• limit time in the sun, especially from 10 a.m. - 2 p.m.
• wear long-sleeved shirts, pants, hats, and sunglasses
• children under 6 months of age: Ask a doctor

Inactive ingredients

Petrolatum, Phytosteryl/Isostearyl/Cetyl/Stearyl/Behenyl Dimer Diloleate, Diisostearyl Malate, Polybutene, Sorbeth-2 Hexaoleate, Synthetic Wax, Hydrogenated Polyisobutene, Flavor (Aroma), Ethylhexyl Methoxycrylene, Butyrospermum Parkii (Shea) Butter, Microcystalline Wax (Cera Microcristallina), Oryzanol, Mica, Helianthus Annus (Sunflower) Seed Oil, Physalis Angulata Extract, Caprylic/Capric Triglyceride, Bisabolol, Siraitia Grosvenorii Fruit Extract, Tocopherol, BHT, Citric Acid, Red 33 (CI 17200), Yellow 5 Lake (CI 19140), Blue 1 Lake (CI 42090), Isopropyl Titanium Triisostearate, Menthol, Limonene, Carvone, Mentha Piperita (Peppermint) Oil, Mentha Viridis (Spearmint) Leaf Oil, Citrus Limone Peel Oil, Pinene, Beta-Caryophyllene, Terpineol, Linalool, Alpha-Terpinene, Camphor, Citral.

Other Information

• protect the product in this container from excessive
heat and direct sun

Questions?

Visit www.prequelskin.com

Purpose

Purpose: Sunscreen

Keep out of reach of children. If product is swallowed, get medical help or contact a Poison Control Center right away.